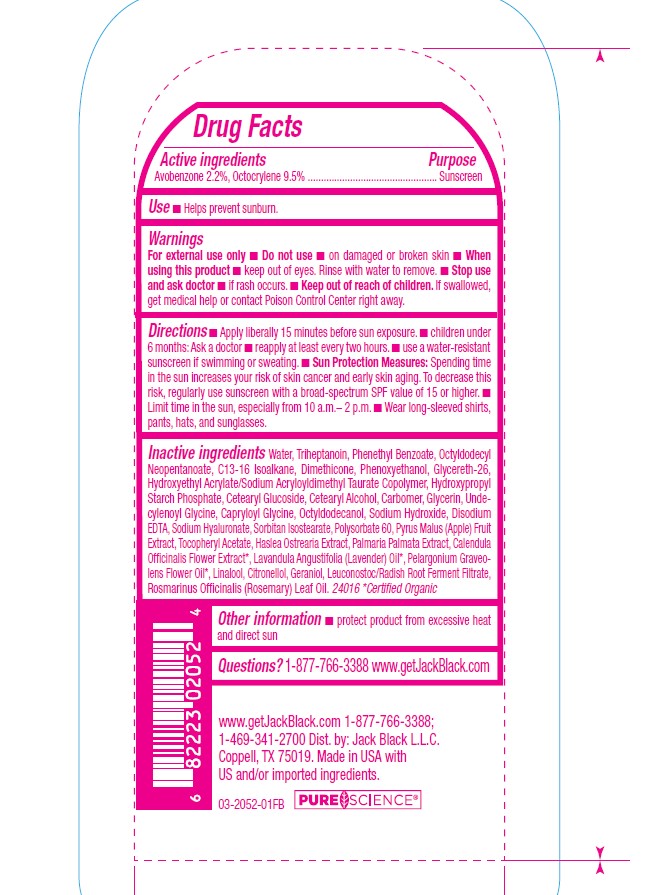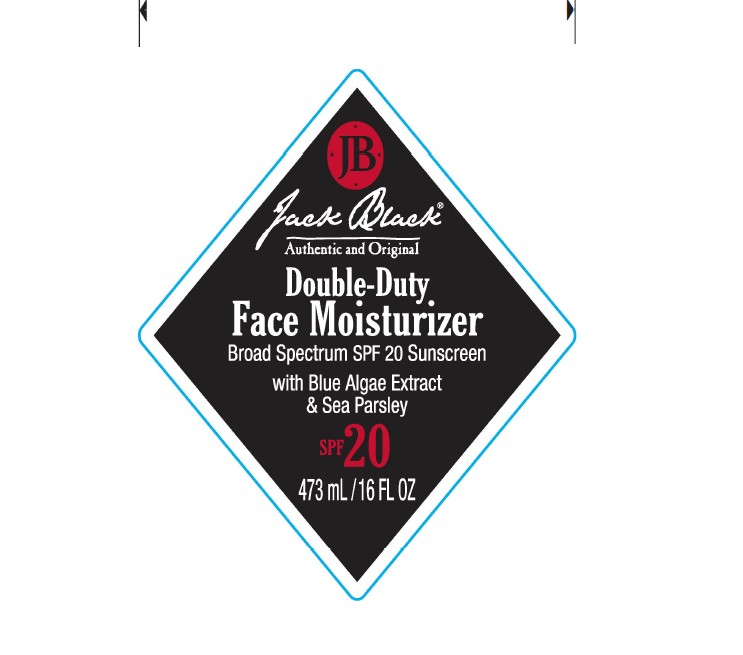 DRUG LABEL: Jack Black Double Duty
NDC: 66738-771 | Form: LOTION
Manufacturer: Jack Black L.L.C.
Category: otc | Type: HUMAN OTC DRUG LABEL
Date: 20250827

ACTIVE INGREDIENTS: OCTOCRYLENE 9.5 g/100 mL; AVOBENZONE 2.2 g/100 mL
INACTIVE INGREDIENTS: PHENOXYETHANOL; PYRUS MALUS (APPLE) FRUIT; HASLEA OSTREARIA; PALMARIA PALMATA; PELARGONIUM GRAVEOLENS FLOWER OIL; LEUCONOSTOC/RADISH ROOT FERMENT FILTRATE; OCTYLDODECYL NEOPENTANOATE; POLYSORBATE 60; CETEARYL ALCOHOL; UNDECYLENOYL GLYCINE; SODIUM HYDROXIDE; CARBOMER; WATER; HYDROXYETHYL ACRYLATE/SODIUM ACRYLOYLDIMETHYL TAURATE COPOLYMER (45000 MPA.S AT 1%); C13-16 ISOPARAFFIN; GLYCERIN; CAPRYLOYL GLYCINE; EDETATE DISODIUM; CALENDULA OFFICINALIS FLOWER; GERANIOL; ROSMARINUS OFFICINALIS (ROSEMARY) LEAF OIL; CETEARYL GLUCOSIDE; SORBITAN ISOSTEARATE; .ALPHA.-TOCOPHEROL ACETATE; LINALOOL; TRIHEPTANOIN; PHENETHYL BENZOATE; OCTYLDODECANOL; SODIUM HYALURONATE; LAVANDULA ANGUSTIFOLIA (LAVENDER) OIL; CITRONELLOL; DIMETHICONE; GLYCERETH-26

Active Ingredients

Avobenzone 2.2%

Octocrylene 9.5%

Purpose

Sunscreen

Uses

Helps prevent sunburn.

Warnings

For external use only

Do not use

• on damaged or broken skin

When using this product

• keep out of eyes. Rinse with water to remove.

Stop use and ask doctor

• if rash occurs

Keep out of reach of children.

If swallowed, get medical help or contact a Poison Control Center right away.

Directions

• Apply liberally 15 minutes before sun exposure. • children under 6 months: Ask a doctor • reapply at least every 2 hours • use a water resistant sunscreen if swimming or sweating. • Sun Protection Measures: Spending time in the sun increases your risk of skin cancer and early skin aging. To decrease this risk, regularly use sunscreen with a broad-spectrum SPF value of 15 or higher. • Limit time in the sun, especially from 10 a.m.– 2 p.m. • Wear long-sleeved shirts, pants, hats, and sunglasses.

Inactive ingredients

Water, Triheptanoin, Phenethyl Benzoate, Octyldodecyl Neopentanoate, C13-16 Isoalkane, Dimethicone, Phenoxyethanol, Glycereth-26, Hydroxyethyl Acrylate/Sodium Acryloyldimethyl Taurate Copolymer, Hydroxypropyl Starch Phosphate, Cetearyl Glucoside, Cetearyl Alcohol, Carbomer, Glycerin, Undecylenoyl Glycine, Capryloyl Glycine, Octyldodecanol, Sodium Hydroxide, Disodium EDTA, Sodium Hyaluronate, Sorbitan Isostearate, Polysorbate 60, Pyrus Malus (Apple) Fruit Extract, Tocopheryl Acetate, Haslea Ostrearia Extract, Palmaria Palmata Extract, Calendula Officinalis Flower Extract, Lavandula Angustifolia (Lavender) Oil, Pelargonium Graveolens Flower Oil, Linalool, Citronellol, Geraniol, Leuconostoc/Radish Root Ferment Filtrate, Rosmarinus Officinalis (Rosemary) Leaf Oil.

Other information

• protect the product in this container from excessive heat and direct sun

Questions?

1-877-766-3388 www.getJackBlack.com

PACKAGE LABEL

Jack Black

Authentic and Original

Double-Duty

Face Moisturizer

Broad Spectrum SPF 20 Sunscreen

with Blue Algae Extract

& Sea Parsley

SPF 20